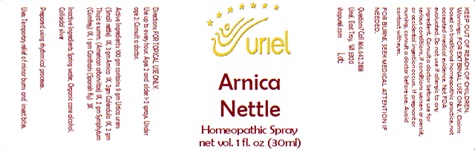 DRUG LABEL: Arnica Nettle
NDC: 48951-1380 | Form: SPRAY
Manufacturer: Uriel Pharmacy Inc.
Category: homeopathic | Type: HUMAN OTC DRUG LABEL
Date: 20241203

ACTIVE INGREDIENTS: URTICA URENS 1 [hp_X]/1 mL; ARNICA MONTANA FLOWER 1 [hp_X]/1 mL; CALENDULA OFFICINALIS FLOWERING TOP 1 [hp_X]/1 mL; THUJA OCCIDENTALIS WHOLE 1 [hp_X]/1 mL; COMFREY ROOT 1 [hp_X]/1 mL; LYTTA VESICATORIA 3 [hp_X]/1 mL
INACTIVE INGREDIENTS: WATER; ALCOHOL; SILVER

Arnica Nettle

INDICATIONS AND USAGE

Directions: FOR TOPICAL USE ONLY.

DOSAGE AND ADMINISTRATION

Use up to every hour. Ages 2 and older: 1-2 sprays. Under age 2: Consult a doctor.

ACTIVE INGREDIENT

Active Ingredients: 100 gm contains: 9 gm Urtica urens (Small nettle) 1X, 3gm Arnica 1X; 2gm Calendula 1X, 2gm Thuja (American arborvitae) 1X, 2gm Symphytum (Comfrey) 1X, 1gm Cantharis (Spanish fly) 3X

INACTIVE INGREDIENT

Inactive Ingredients: Spring water, Organic cane alcohol, Colloidal silver

Prepared using rhythmical processes.

PURPOSE

Uses: Temporary relief of minor burns and insect bites.

KEEP OUT OF REACH OF CHILDREN.

WARNINGS

Warnings: FOR EXTERNAL USE ONLY. Claims based on traditional homeopathic practice, not accepted medical evidence. Not FDA evaluated. Do not use if allergic to any ingredient. Consult a doctor before use for serious conditions, if conditions worsen or persist, or accidental ingestion occurs. If pregnant or nursing, consult a doctor before use. Avoid contact with eyes. Do not use if safety seals on box are broken or missing.
FOR BURNS, SEEK MEDICAL ATTENTION IF NEEDED.

QUESTIONS

Questions? Call 866.642.2858 Uriel, East Troy, WI 53120 shopuriel.com Lot: